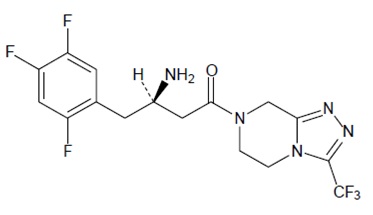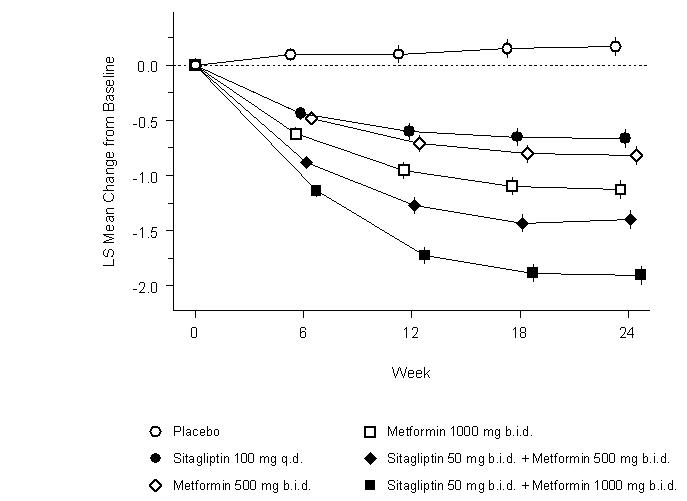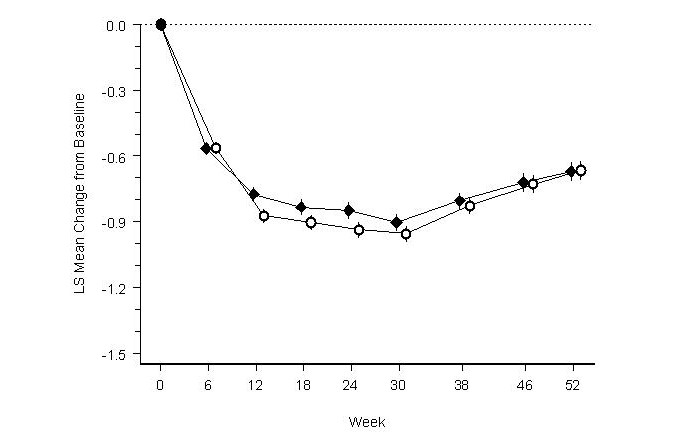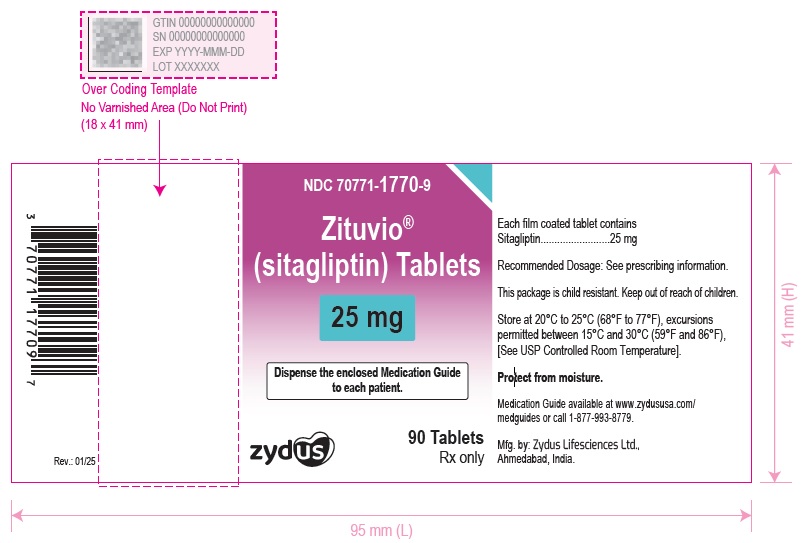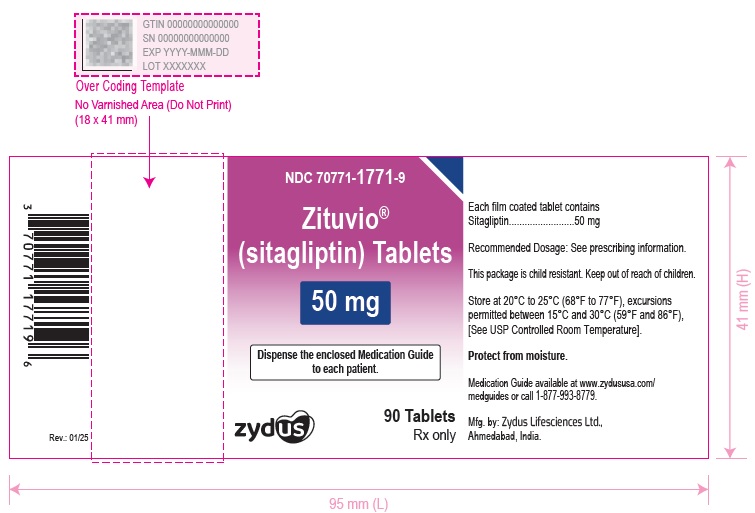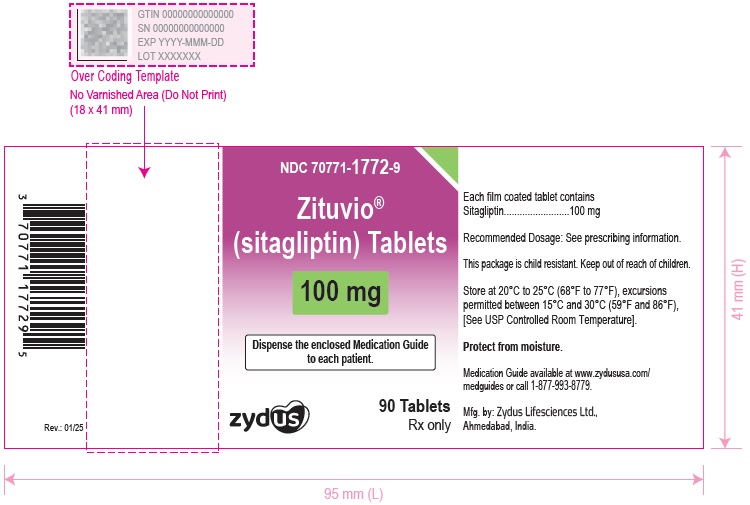 DRUG LABEL: ZITUVIO
NDC: 70771-1770 | Form: TABLET
Manufacturer: Zydus Lifesciences Limited
Category: prescription | Type: HUMAN PRESCRIPTION DRUG LABEL
Date: 20250131

ACTIVE INGREDIENTS: SITAGLIPTIN 25 mg/1 1
INACTIVE INGREDIENTS: POVIDONE, UNSPECIFIED; CROSCARMELLOSE SODIUM; MAGNESIUM STEARATE; MALIC ACID; POLYETHYLENE GLYCOL 3350; POLYVINYL ALCOHOL, UNSPECIFIED; TALC; TITANIUM DIOXIDE; ANHYDROUS DIBASIC CALCIUM PHOSPHATE; MICROCRYSTALLINE CELLULOSE; SILICON DIOXIDE

HIGHLIGHTS OF PRESCRIBING INFORMATION

These highlights do not include all the information needed to use ZITUVIO safely and effectively. See full prescribing information for ZITUVIO.
ZITUVIO ® (sitagliptin) tablets, for oral use
Initial U.S. Approval: 2006

1 INDICATIONS AND USAGE

ZITUVIO is a dipeptidyl peptidase-4 (DPP-4) inhibitor indicated as an adjunct to diet and exercise to improve glycemic control in adults with type 2 diabetes mellitus. (1)

Limitations of Use:

- ZITUVIO is not recommended in patients with type 1 diabetes mellitus. (1)
- ZITUVIO has not been studied in patients with a history of pancreatitis. (1)

2 DOSAGE AND ADMINISTRATION

The recommended dosage of ZITUVIO is 100 mg orally once daily. ZITUVIO can be taken with or without food. (2.1)

Dosage adjustment is recommended for patients with eGFR less than 45 mL/min/1.73 m^2. (2.2)

Dosage Adjustment in Patients with Renal Impairment (2.2)
eGFR greater than or equal to 30 mL/min/1.73 m^2 to less than 45 mL/min/1.73 m^2 | eGFR less than 30 mL/min/1.73 m^2 (including patients with end stage renal disease [ESRD] on dialysis)
50 mg once daily | 25 mg once daily

3 DOSAGE FORMS AND STRENGTHS

Tablets: 100 mg, 50 mg, and 25 mg (3)

4 CONTRAINDICATIONS

History of a serious hypersensitivity reaction to sitagliptin or any of the excipients in ZITUVIO, such as anaphylaxis or angioedema (4)

5 WARNINGS AND PRECAUTIONS

- Pancreatitis: There have been postmarketing reports of acute pancreatitis, including fatal and non-fatal hemorrhagic or necrotizing pancreatitis. If pancreatitis is suspected, promptly discontinue ZITUVIO. (5.1)
- Heart failure: Heart failure has been observed with two other members of the DPP-4 inhibitor class. Consider risks and benefits of ZITUVIO in patients who have known risk factors for heart failure. Monitor patients for signs and symptoms. (5.2)
- Acute Renal Failure:Has been reported postmarketing, sometimes requiring dialysis. Assessment of renal function is recommended prior to initiating ZITUVIO and periodically thereafter. (5.3)
- Hypoglycemia with Concomitant Use with Insulin or Insulin Secretagogues: Increased risk of hypoglycemia when used in combination with insulin and/or an insulin secretagogue. Lower dose of insulin or insulin secretagogue may be required. (5.4)
- Hypersensitivity Reactions: There have been postmarketing reports of serious allergic and hypersensitivity reactions in patients treated with sitagliptin such as anaphylaxis, angioedema, and exfoliative skin conditions including Stevens-Johnson syndrome. Promptly stop ZITUVIO, assess for other potential causes, institute appropriate monitoring and treatment. (5.5)
- Severe and Disabling Arthralgia: Has been reported in patients taking DPP-4 inhibitors. Consider as a possible cause for severe joint pain and discontinue drug if appropriate. (5.6)
- Bullous Pemphigoid: There have been postmarketing reports requiring hospitalization in patients taking DPP-4 inhibitors. Tell patients to report development of blisters or erosions. If bullous pemphigoid is suspected, discontinue ZITUVIO. (5.7)

6 ADVERSE REACTIONS

Most common adverse reactions (incidence ≥5%) are: upper respiratory tract infection, nasopharyngitis and headache. In the add-on to sulfonylurea and add-on to insulin studies, hypoglycemia was also more commonly reported in patients treated with sitagliptin compared to placebo. (6.1)

To report SUSPECTED ADVERSE REACTIONS, contact Zydus Pharmaceuticals (USA) Inc. at 1-877-993-8779 or FDA at 1-800-FDA-1088 or www.fda.gov/medwatch.

FULL PRESCRIBING INFORMATION

1 INDICATIONS AND USAGE

ZITUVIO® is indicated as an adjunct to diet and exercise to improve glycemic control in adults with type 2 diabetes mellitus.

Limitations of Use

ZITUVIO is not recommended in patients with type 1 diabetes mellitus.

ZITUVIO has not been studied in patients with a history of pancreatitis. It is unknown whether patients with a history of pancreatitis are at increased risk for the development of pancreatitis while using ZITUVIO. [see Warnings and Precautions (5.1)].

2 DOSAGE AND ADMINISTRATION

2.1 Recommended Dosage

The recommended dosage of ZITUVIO is 100 mg orally once daily. ZITUVIO can be taken with or without food.

2.2 Recommendations for Use in Renal Impairment

Assess renal function prior to initiation of ZITUVIO and periodically thereafter.

For patients with an estimated glomerular filtration rate [eGFR] greater than or equal to 45 mL/min/1.73 m^2to less than 90 mL/min/1.73 m^2, no dosage adjustment for ZITUVIO is required.

For patients with moderate renal impairment (eGFR greater than or equal to 30 mL/min/1.73 m^2to less than 45 mL/min/1.73 m^2), the dosage of ZITUVIO is 50 mg once daily.

For patients with severe renal impairment (eGFR less than 30 mL/min/1.73 m^2) or with end-stage renal disease (ESRD) requiring hemodialysis or peritoneal dialysis, the dosage of ZITUVIO is 25 mg once daily. ZITUVIO may be administered without regard to the timing of dialysis.

3 DOSAGE FORMS AND STRENGTHS

- 100 mg tablets are beige, round, biconvex, film coated tablets debossed with "12" on one side and "42" on the other side.
- 50 mg tablets are pale yellow, round, biconvex, film coated tablets debossed with "12" on one side and "41" on the other side.
- 25 mg tablets are white to off white, round, biconvex, film coated tablets debossed with "12" on one side and "40" on the other side.

4 CONTRAINDICATIONS

ZITUVIO is contraindicated in patients with a history of a serious hypersensitivity reaction to sitagliptin or any of the excipients in ZITUVIO. Serious hypersensitivity reactions, including anaphylaxis and angioedema have been reported with sitagliptin. [see Warnings and Precautions (5.5); Adverse Reactions (6.2)].

5 WARNINGS AND PRECAUTIONS

5.1 Pancreatitis

There have been postmarketing reports of acute pancreatitis, including fatal and non-fatal hemorrhagic or necrotizing pancreatitis, in patients taking sitagliptin. After initiation of ZITUVIO, patients should be observed carefully for signs and symptoms of pancreatitis. If pancreatitis is suspected, ZITUVIO should promptly be discontinued and appropriate management should be initiated. It is unknown whether patients with a history of pancreatitis are at increased risk for the development of pancreatitis while using ZITUVIO.

5.2 Heart Failure

An association between dipeptidyl peptidase-4 (DPP-4) inhibitor treatment and heart failure has been observed in cardiovascular outcomes trials for two other members of the DPP-4 inhibitor class. These trials evaluated patients with type 2 diabetes mellitus and atherosclerotic cardiovascular disease.

Consider the risks and benefits of ZITUVIO prior to initiating treatment in patients at risk for heart failure, such as those with a prior history of heart failure and a history of renal impairment and observe these patients for signs and symptoms of heart failure during therapy. Advise patients of the characteristic symptoms of heart failure and to immediately report such symptoms. If heart failure develops, evaluate and manage according to current standards of care and consider discontinuation of ZITUVIO.

5.3 Acute Renal Failure

There have been postmarketing reports of worsening renal function, including acute renal failure, sometimes requiring dialysis. A subset of these reports involved patients with renal impairment, some of whom were prescribed inappropriate doses of sitagliptin. A return to baseline levels of renal impairment has been observed with supportive treatment and discontinuation of potentially causative agents. Consideration can be given to cautiously reinitiating ZITUVIO if another etiology is deemed likely to have precipitated the acute worsening of renal function.

Assessment of renal function is recommended prior to initiating ZITUVIO and periodically thereafter. A dosage adjustment is recommended in patients with moderate or severe renal impairment and in patients with ESRD requiring hemodialysis or peritoneal dialysis. [see Dosage and Administration (2.2); Use in Specific Populations (8.6)].

5.4 Hypoglycemia with Concomitant Use with Insulin or Insulin Secretagogues

When sitagliptin was used in combination with insulin or insulin secretagogues (e.g., sulfonylurea), medications known to cause hypoglycemia, the incidence of hypoglycemia was increased over that of placebo used in combination with a sulfonylurea or with insulin. [see Adverse Reactions (6.1)]. Therefore, a lower dose of sulfonylurea or insulin may be required to reduce the risk of hypoglycaemia when used in combination with ZITUVIO. [see Drug Interactions (7.1)].

5.5 Hypersensitivity Reactions

There have been postmarketing reports of serious hypersensitivity reactions in patients treated with sitagliptin. These reactions include anaphylaxis, angioedema, and exfoliative skin conditions including Stevens-Johnson syndrome. Onset of these reactions occurred within the first 3 months after initiation of treatment with sitagliptin, with some reports occurring after the first dose. If a hypersensitivity reaction is suspected, discontinue ZITUVIO, assess for other potential causes for the event, and institute alternative treatment for diabetes. [see Adverse Reactions (6.2)].

Angioedema has also been reported with other DPP-4 inhibitors. Use caution in a patient with a history of angioedema with another DPP-4 inhibitor because it is unknown whether such patients will be predisposed to angioedema with ZITUVIO.

5.6 Severe and Disabling Arthralgia

There have been postmarketing reports of severe and disabling arthralgia in patients taking DPP-4 inhibitors. The time to onset of symptoms following initiation of drug therapy varied from one day to years. Patients experienced relief of symptoms upon discontinuation of the medication. A subset of patients experienced a recurrence of symptoms when restarting the same drug or a different DPP-4 inhibitor. Consider DPP-4 inhibitors as a possible cause for severe joint pain and discontinue drug if appropriate.

5.7 Bullous Pemphigoid

Postmarketing cases of bullous pemphigoid requiring hospitalization have been reported with DPP-4 inhibitor use. In reported cases, patients typically recovered with topical or systemic immunosuppressive treatment and discontinuation of the DPP-4 inhibitor. Tell patients to report development of blisters or erosions while receiving ZITUVIO. If bullous pemphigoid is suspected, ZITUVIO should be discontinued and referral to a dermatologist should be considered for diagnosis and appropriate treatment.

6 ADVERSE REACTIONS

The following adverse reactions are also discussed elsewhere in the prescribing information:

- Pancreatitis [see Warnings and Precautions (5.1)]
- Heart Failure [see Warnings and Precautions (5.2)]
- Acute Renal Failure [see Warnings and Precautions (5.3)]
- Hypoglycemia with Concomitant Use with Insulin or Insulin Secretagogues [see Warnings and Precautions (5.4)]
- Hypersensitivity Reactions [see Warnings and Precautions (5.5)]
- Severe and Disabling Arthralgia [see Warnings and Precautions (5.6)]
- Bullous Pemphigoid [see Warnings and Precautions (5.7)]

6.1 Clinical Trials Experience

Because clinical trials are conducted under widely varying conditions, adverse reaction rates observed in the clinical trials of a drug cannot be directly compared to rates in the clinical trials of another drug and may not reflect the rates observed in practice.

Common Adverse Reactions

In controlled clinical trials as both monotherapy and combination therapy with metformin, pioglitazone, or rosiglitazone and metformin, the overall incidence of adverse reactions, hypoglycemia, and discontinuation of therapy due to clinical adverse reactions with sitagliptin were similar to placebo. In combination with glimepiride, with or without metformin, the overall incidence of clinical adverse reactions with sitagliptin was higher than with placebo, in part related to a higher incidence of hypoglycemia (see Table 3); the incidence of discontinuation due to clinical adverse reactions was similar to placebo.

Two placebo-controlled monotherapy trials, one of 18- and one of 24-week duration, included patients treated with sitagliptin 100 mg daily, sitagliptin 200 mg daily, and placebo. Five placebo-controlled add-on combination therapy trials were also conducted: one with metformin; one with pioglitazone; one with metformin and rosiglitazone; one with glimepiride (with or without metformin); and one with insulin (with or without metformin). In these trials, patients with inadequate glycemic control on a stable dosage of the background therapy were randomized to add-on therapy with sitagliptin 100 mg daily or placebo. The adverse reactions, excluding hypoglycemia, reported in ≥5% of patients treated with sitagliptin 100 mg daily and more commonly than in patients treated with placebo, are shown in Table 1 for the clinical trials of at least 18 weeks duration. Incidences of hypoglycemia are shown in Table 3.

Table 1: Placebo-Controlled Clinical Trials of Sitagliptin Monotherapy or Add-on Combination Therapy with Pioglitazone, Metformin + Rosiglitazone, or Glimepiride +/-Metformin: Adverse Reactions (Excluding Hypoglycemia) Reported in ≥5% of Patients and More Commonly than in Patients Given Placebo [Intent-to-treat population]
 | Number of Patients (%)
Monotherapy (18 or 24 weeks) | Sitagliptin 100 mg | Placebo
 | N = 443 | N = 363
Nasopharyngitis | 23 (5.2) | 12 (3.3)
Combination with Pioglitazone (24 weeks) | Sitagliptin 100 mg + Pioglitazone | Placebo + Pioglitazone
 | N = 175 | N = 178
Upper Respiratory Tract Infection | 11 (6.3) | 6 (3.4)
Headache | 9 (5.1) | 7 (3.9)
Combination with Metformin + Rosiglitazone (18 weeks) | Sitagliptin 100 mg + Metformin + Rosiglitazone | Placebo + Metformin + Rosiglitazone
 | N = 181 | N = 97
Upper Respiratory Tract Infection | 10 (5.5) | 5 (5.2)
Nasopharyngitis | 11 (6.1) | 4 (4.1)
Combination with Glimepiride (+/- Metformin) (24 weeks) | Sitagliptin 100 mg + Glimepiride (+/- Metformin) | Placebo + Glimepiride (+/- Metformin)
 | N = 222 | N = 219
Nasopharyngitis | 14 (6.3) | 10 (4.6)
Headache | 13 (5.9) | 5 (2.3)

In the 24-week trial of patients receiving sitagliptin as add-on combination therapy with metformin, there were no adverse reactions reported in ≥5% of patients and more commonly than in patients given placebo.

In the 24-week trial of patients receiving sitagliptin as add-on therapy to insulin (with or without metformin), there were no adverse reactions reported in ≥5% of patients and more commonly than in patients given placebo, except for hypoglycemia (see Table 3).

In the trial of sitagliptin as add-on combination therapy with metformin and rosiglitazone (Table 1), through Week 54 the adverse reactions reported in ≥5% of patients treated with sitagliptin and more commonly than in patients treated with placebo were: upper respiratory tract infection (sitagliptin, 15.5%; placebo, 6.2%), nasopharyngitis (11%, 9.3%), peripheral edema (8.3%, 5.2%), and headache (5.5%, 4.1%).

In an additional, 24-week, placebo-controlled factorial trial of initial therapy with sitagliptin in combination with metformin, the adverse reactions reported in ≥5% of patients are shown in Table 2.

Table 2: Initial Therapy with Combination of Sitagliptin and Metformin: Adverse Reactions Reported in ≥5% of Patients Receiving Combination Therapy (and Greater than in Patients Receiving Metformin alone, Sitagliptin alone, and Placebo) [Intent-to-treat population.]
 | Number of Patients (%)
 | Placebo | Sitagliptin 100 mg QD | Metformin HCl 500 or 1,000 mg bid [Data pooled for the patients given the lower and higher doses of metformin.] | Sitagliptin 50 mg bid + Metformin HCl 500 or 1,000 mg bid
 | N = 176 | N = 179 | N = 364 | N = 372
Upper Respiratory Infection | 9 (5.1) | 8 (4.5) | 19 (5.2) | 23 (6.2)
Headache | 5 (2.8) | 2 (1.1) | 14 (3.8) | 22 (5.9)

In a 24-week trial of initial therapy with sitagliptin in combination with pioglitazone, there were no adverse reactions reported in ≥5% of patients and more commonly than in patients given pioglitazone alone.

Other Adverse Reactions

Hypoglycemia

In the above trials (N=9), adverse reactions of hypoglycemia were based on all reports of symptomatic hypoglycemia. A concurrent blood glucose measurement was not required although most (74%) reports of hypoglycemia were accompanied by a blood glucose measurement ≤70 mg/dL. When sitagliptin was coadministered with a sulfonylurea or with insulin, the percentage of patients with at least one adverse reaction of hypoglycemia was higher than in the corresponding placebo group (Table 3).

Table 3: Incidence and Rate of Hypoglycemia [Adverse reactions of hypoglycemia were based on all reports of symptomatic hypoglycemia; a concurrent glucose measurement was not required; intent-to-treat population.] in Placebo-Controlled Clinical Trials when Sitagliptin was used as Add-On Therapy to Glimepiride (with or without Metformin) or Insulin (with or without Metformin)
Add-On to Glimepiride (+/- Metformin) (24 weeks) | Sitagliptin 100 mg + Glimepiride (+/- Metformin) | Placebo + Glimepiride (+/- Metformin)
 | N = 222 | N = 219
Overall (%) | 27 (12.2) | 4 (1.8)
Rate (episodes/patient-year) [Based on total number of events (i.e., a single patient may have had multiple events).] | 0.59 | 0.24
Severe (%) [Severe events of hypoglycemia were defined as those events requiring medical assistance or exhibiting depressed level/loss of consciousness or seizure.] | 0 (0) | 0 (0)
Add-On to Insulin (+/- Metformin) (24 weeks) | Sitagliptin 100 mg + Insulin (+/- Metformin) | Placebo + Insulin (+/- Metformin)
 | N = 322 | N = 319
Overall (%) | 50 (15.5) | 25 (7.8)
Rate (episodes/patient-year) | 1.06 | 0.51
Severe (%) | 2 (0.6) | 1 (0.3)

In a pooled analysis of the two monotherapy trials, the add-on to metformin trial, and the add-on to pioglitazone trial, the overall incidence of adverse reactions of hypoglycemia was 1.2% in patients treated with sitagliptin 100 mg and 0.9% in patients treated with placebo.

In the trial of sitagliptin as add-on combination therapy with metformin and rosiglitazone, the overall incidence of hypoglycemia was 2.2% in patients given add-on sitagliptin and 0% in patients given add-on placebo through Week 18. Through Week 54, the overall incidence of hypoglycemia was 3.9% in patients given add-on sitagliptin sitagliptin and 1% in patients given add-on placebo.

In the 24-week, placebo-controlled factorial trial of initial therapy with sitagliptin in combination with metformin, the incidence of hypoglycemia was 0.6% in patients given placebo, 0.6% in patients given sitagliptin alone, 0.8% in patients given metformin alone, and 1.6% in patients given sitagliptin in combination with metformin.

In the trial of sitagliptin as initial therapy with pioglitazone, one patient taking ZITUVIO experienced a severe episode of hypoglycemia. There were no severe hypoglycemia episodes reported in other trials except in the trial involving coadministration with insulin.

In an additional, 30-week placebo-controlled, trial of patients with type 2 diabetes mellitus inadequately controlled with metformin comparing the maintenance of sitagliptin 100 mg versus withdrawal of sitagliptin when initiating basal insulin therapy, the event rate and incidence of documented symptomatic hypoglycemia (blood glucose measurement ≤70 mg/dL) did not differ between the sitagliptin and placebo groups.

Gastrointestinal Adverse Reactions

In a pooled analysis of the two monotherapy trials, the add-on to metformin trial, and the add-on to pioglitazone trial, the incidence of selected gastrointestinal adverse reactions in patients treated with sitagliptin was as follows: abdominal pain (ZITUVIO 100 mg, 2.3%; placebo, 2.1%),

nausea (1.4%, 0.6%), and diarrhea (3%, 2.3%).

Pancreatitis

In a pooled analysis of 19 double-blind clinical trials that included data from 10,246 patients randomized to receive sitagliptin 100 mg/day (N=5,429) or corresponding (active or placebo) control (N=4,817), the incidence of acute pancreatitis was 0.1 per 100 patient-years in each group (4 patients with an event in 4,708 patient-years for sitagliptin and 4 patients with an event in 3,942 patient-years for control).

Vital Sign and Electrocardiogram (EGC) Changes

No clinically meaningful changes in vital signs or in ECG (including in QTc interval) were observed in patients treated with sitagliptin

Laboratory Tests

Across clinical trials, the incidence of laboratory adverse reactions was similar in patients treated with sitagliptin 100 mg compared to patients treated with placebo. A small increase in white blood cell count (WBC) was observed due to an increase in neutrophils. This increase in WBC (of approximately 200 cells/microL vs placebo, in four pooled placebo-controlled clinical trials, with a mean baseline WBC count of approximately 6,600 cells/microL) is not considered to be clinically relevant. In a 12-week trial of 91 patients with chronic renal insufficiency, 37 patients with moderate renal insufficiency were randomized to sitagliptin 50 mg daily, while 14 patients with the same magnitude of renal impairment were randomized to placebo. Mean (SE) increases in serum creatinine were observed in patients treated with sitagliptin [0.12 mg/dL (0.04)] and in patients treated with placebo [0.07 mg/dL (0.07)]. The clinical significance of this added increase in serum creatinine relative to placebo is not known.

6.2 Postmarketing Experience

The following adverse reactions have been identified during post-approval use of sitagliptin as monotherapy and/or in combination with other antihyperglycemic agents. Because these reactions are reported voluntarily from a population of uncertain size, it is generally not possible to reliably estimate their frequency or establish a causal relationship to drug exposure.

Skin and subcutaneous tissue disorders: hypersensitivity reactions including anaphylaxis, angioedema, rash, urticaria, cutaneous vasculitis, bullous pemphigoid, and exfoliative skin conditions including Stevens-Johnson syndrome

Hepatobiliary disorders: hepatic enzyme elevations

Gastrointestinal disorders: acute pancreatitis, including fatal and non-fatal hemorrhagic and necrotizing pancreatitis, constipation; vomiting, mouth ulceration, and stomatitis

Renal and urinary disorders: worsening renal function, including acute renal failure (sometimes requiring dialysis), and tubulointerstitial nephritis

Musculoskeletal and connective tissue disorders: severe and disabling arthralgia; myalgia; pain in extremity; back pain; pruritus; rhabdomyolysis

Nervous system disorders: headache

7 DRUG INTERACTIONS

7.1 Insulin Secretagogues or Insulin

Sitagliptin lowers blood glucose in patients with type 2 diabetes mellitus. Coadministration of ZITUVIO with an insulin secretagogue (e.g., sulfonylurea) or insulin may require lower doses of the insulin secretagogue or insulin to reduce the risk of hypoglycemia. [see Warnings and Precautions (5.4) ].

8 USE IN SPECIFIC POPULATIONS

8.1 Pregnancy

Risk Summary

The limited available data with sitagliptin in pregnant women are not sufficient to inform a drug-associated risk for major birth defects and miscarriage. There are risks to the mother and fetus associated with poorly controlled diabetes in pregnancy [see Clinical Considerations]. No adverse developmental effects were observed when sitagliptin was administered to pregnant rats and rabbits during organogenesis at oral doses up to 30-times and 20-times, respectively, the 100 mg clinical dose, based on AUC [see Data].

The estimated background risk of major birth defects is 6 to 10% in women with pre-gestational diabetes with a hemoglobin A1c (A1C) >7% and has been reported to be as high as 20 to 25% in women with a A1C >10%. In the U.S. general population, the estimated background risk of major birth defects and miscarriage in clinically recognized pregnancies is 2 to 4% and 15 to 20%, respectively.

Clinical Considerations

Disease-Associated Maternal and/or Embryo/Fetal Risk

Poorly controlled diabetes in pregnancy increases the maternal risk for diabetic ketoacidosis, pre-eclampsia, spontaneous abortions, preterm delivery, and delivery complications. Poorly controlled diabetes increases the fetal risk for major birth defects, still birth, and macrosomia related morbidity.

Data

Animal Data

In embryo-fetal development studies, sitagliptin administered to pregnant rats and rabbits during organogenesis (gestation day 6 to 20) did not adversely affect developmental outcomes at oral doses up to 250 mg/kg (30-times the 100 mg clinical dose) and 125 mg/kg (20-times the 100 mg clinical dose), respectively, based on AUC. Higher doses in rats associated with maternal toxicity increased the incidence of rib malformations in offspring at 1,000 mg/kg, or approximately 100-times the clinical dose, based on AUC. Placental transfer of sitagliptin was observed in pregnant rats and rabbits.

Sitagliptin administered to female rats from gestation day 6 to lactation day 21 caused no functional or behavioral toxicity in offspring of rats at doses up to 1,000 mg/kg.

8.2 Lactation

Risk Summary

There is no information regarding the presence of sitagliptin in human milk, the effects on the breastfed infant, or the effects on milk production. Sitagliptin is present in rat milk and therefore possibly present in human milk [see Data]. The developmental and health benefits of breastfeeding should be considered along with the mother's clinical need for ZITUVIO and any potential adverse effects on the breastfed infant from ZITUVIO or from the underlying maternal condition.

Data

Sitagliptin is secreted in the milk of lactating rats at a milk to plasma ratio of 4:1.

8.4 Pediatric Use

The safety and effectiveness of ZITUVIO have not been established in pediatric patients.

Pediatric information describing clinical trials in which efficacy was not demonstrated is approved for Merck Sharp and Dohme's JANUVIA (sitagliptin) tablets. However, due to Merck Sharp and Dohme's marketing exclusivity rights, this drug product is not labeled with that information.

8.5 Geriatric Use

Of the total number of subjects (N=3,884) in pre-approval clinical safety and efficacy trials of sitagliptin, 725 patients were 65 years and over, while 61 patients were 75 years and over. No overall differences in safety or effectiveness of sitagliptin have been observed between

patients 65 years and over and younger patients.

Because sitagliptin is substantially excreted by the kidney, and because aging can be associated with reduced renal function, renal function should be assessed more frequently in elderly patients [see Dosage and Administration (2.2), Warnings and Precautions (5.3)]

8.6 Renal Impairment

Sitagliptin is excreted by the kidney, and sitagliptin exposure is increased in patients with renal impairment. Lower dosages are recommended in patients with eGFR less than 45 mL/min/1.73 m^2(moderate and severe renal impairment, as well as in ESRD patients requiring dialysis). [see Dosage and Administration (2.2); Clinical Pharmacology (12.3)].

10 OVERDOSAGE

In the event of an overdose with ZITUVIO, consider contacting the Poison Help line (1-800-222-1222) or a medical toxicologist for additional overdosage management recommendations. Employ the usual supportive measures dictated by the patient's clinical status. Per clinical judgment, consider removal of unabsorbed material from the gastrointestinal tract and clinical monitoring (including obtaining an ECG).

Sitagliptin is modestly dialyzable. In clinical trials, approximately 13.5% of the dose was removed over a 3-to 4-hour hemodialysis session. Prolonged hemodialysis may be considered if clinically appropriate. It is not known if sitagliptin is dialyzable by peritoneal dialysis.

11 DESCRIPTION

ZITUVIO Tablets contain sitagliptin free base, an orally active inhibitor of the DPP-4 enzyme.

Sitagliptin free base is described chemically as 7-[(3R)-3-amino-1-oxo-4-(2,4,5-trifluorophenyl)butyl]-5,6,7,8-tetrahydro-3-(trifluoromethyl)-1,2,4-triazolo[4,3-a]pyrazine.

The empirical formula is C16H15F6N5O and the molecular weight is 407.31. The structural formula is:

Sitagliptin free base is a white to off-white, non-hygroscopic powder. Sitagliptin free base is soluble in methanol and slightly soluble in water.

Each film coated tablet of ZITUVIO contains sitagliptin free base 25 mg, 50 mg, or 100 mg as active ingredient and the following inactive ingredients: anhydrous dibasic calcium phosphate, colloidal silicon dioxide, croscarmellose sodium, malic acid, magnesium stearate, microcrystalline cellulose, and povidone. In addition, the film coating contains the following inactive ingredients: polyethylene glycol, polyvinyl alcohol, talc, and titanium dioxide. The 50 mg tablet's film coating also contains ferrosoferric oxide and iron oxide yellow. The 100 mg tablet's film coating also contains FD&C Yellow #6 Aluminum Lake and iron oxide yellow.

12 CLINICAL PHARMACOLOGY

12.1 Mechanism of Action

Sitagliptin is a DPP-4 inhibitor, which is believed to exert its actions in patients with type 2 diabetes mellitus by slowing the inactivation of incretin hormones. Concentrations of the active intact hormones are increased by sitagliptin, thereby increasing and prolonging the action of these hormones. Incretin hormones, including glucagon-like peptide-1 (GLP-1) and glucose-dependent insulinotropic polypeptide (GIP), are released by the intestine throughout the day, and levels are increased in response to a meal. These hormones are rapidly inactivated by the enzyme, DPP-4. The incretins are part of an endogenous system involved in the physiologic regulation of glucose homeostasis. When blood glucose concentrations are normal or elevated, GLP-1 and GIP increase insulin synthesis and release from pancreatic beta cells by intracellular signaling pathways involving cyclic AMP. GLP-1 also lowers glucagon secretion from pancreatic alpha cells, leading to reduced hepatic glucose production. By increasing and prolonging active incretin levels, sitagliptin increases insulin release and decreases glucagon levels in the circulation in a glucose-dependent manner. Sitagliptin demonstrates selectivity for DPP-4 and does not inhibit DPP-8 or DPP-9 activity in vitro at concentrations approximating those from therapeutic doses.

12.2 Pharmacodynamics

General

In patients with type 2 diabetes mellitus, administration of sitagliptin led to inhibition of DPP-4 enzyme activity for a 24-hour period. After an oral glucose load or a meal, this DPP-4 inhibition resulted in a 2-to 3-fold increase in circulating levels of active GLP-1 and GIP, decreased glucagon concentrations, and increased responsiveness of insulin release to glucose, resulting in higher C-peptide and insulin concentrations. The rise in insulin with the decrease in glucagon was associated with lower fasting glucose concentrations and reduced glucose excursion following an oral glucose load or a meal.

In studies with healthy subjects, sitagliptin did not lower blood glucose or cause hypoglycemia.

Sitagliptin and Metformin hydrochloride Coadministration

In a two-day study in healthy subjects, sitagliptin alone increased active GLP-1 concentrations, whereas metformin alone increased active and total GLP-1 concentrations to similar extents. Coadministration of sitagliptin and metformin had an additive effect on active GLP-1 concentrations. Sitagliptin, but not metformin, increased active GIP concentrations. It is unclear how these findings relate to changes in glycemic control in patients with type 2 diabetes mellitus.

Cardiac Electrophysiology

In a randomized, placebo-controlled crossover study, 79 healthy subjects were administered a single oral dose of sitagliptin 100 mg, sitagliptin 800 mg (8 times the recommended dose), and placebo. At the recommended dose of 100 mg, there was no effect on the QTc interval obtained at the peak plasma concentration, or at any other time during the study. Following the 800 mg dose, the maximum increase in the placebo-corrected mean change in QTc from baseline was observed at 3 hours postdose and was 8 msec. This increase is not considered to be clinically significant. At the 800 mg dose, peak sitagliptin plasma concentrations were approximately 11 times higher than the peak concentrations following a 100-mg dose.

In patients with type 2 diabetes mellitus administered sitagliptin 100 mg (N=81) or sitagliptin 200 mg (N=63) daily, there were no meaningful changes in QTc interval based on ECG data obtained at the time of expected peak plasma concentration.

12.3 Pharmacokinetics

The pharmacokinetics of sitagliptin have been extensively characterized in healthy subjects and patients with type 2 diabetes mellitus. Following a single oral 100-mg dose to healthy volunteers, mean plasma AUC of sitagliptin was 8.52 μM•hr, Cmax was 950 nM, and apparent terminal half-life (t1/2) was 12.4 hours. Plasma AUC of sitagliptin increased in a dose-proportional manner and increased approximately 14% following 100 mg doses at steady-state compared to the first dose. The intra-subject and inter-subject coefficients of variation for sitagliptin AUC were small (5.8% and 15.1%). The pharmacokinetics of sitagliptin was generally similar in healthy subjects and in patients with type 2 diabetes mellitus.

Absorption

After oral administration of a 100 mg dose to healthy subjects, sitagliptin was rapidly absorbed with peak plasma concentrations (median Tmax) occurring 1 to 4 hours postdose. The absolute bioavailability of sitagliptin is approximately 87%.

Effect of Food

Coadministration of a high-fat meal with sitagliptin had no effect on the pharmacokinetics of sitagliptin.

Distribution

The mean volume of distribution at steady state following a single 100-mg intravenous dose of sitagliptin to healthy subjects is approximately 198 liters. The fraction of sitagliptin reversibly bound to plasma proteins is low (38%).

Elimination

Approximately 79% of sitagliptin is excreted unchanged in the urine with metabolism being a minor pathway of elimination. The apparent terminal t1/2 following a 100 mg oral dose of sitagliptin was approximately 12.4 hours and renal clearance was approximately 350 mL/min.

Metabolism

Following a [^14C] sitagliptin oral dose, approximately 16% of the radioactivity was excreted as metabolites of sitagliptin. Six metabolites were detected at trace levels and are not expected to contribute to the plasma DPP-4 inhibitory activity of sitagliptin. In vitro studies indicated that the primary enzyme responsible for the limited metabolism of sitagliptin was CYP3A4, with contribution from CYP2C8.

Excretion

Following administration of an oral [^14C] sitagliptin dose to healthy subjects, approximately 100% of the administered radioactivity was eliminated in feces (13%) or urine (87%) within one week of dosing.

Elimination of sitagliptin occurs primarily via renal excretion and involves active tubular secretion. Sitagliptin is a substrate for human organic anion transporter-3 (hOAT-3), which may be involved in the renal elimination of sitagliptin. The clinical relevance of hOAT-3 in sitagliptin transport has not been established. Sitagliptin is also a substrate of P-glycoprotein (P-gp), which may also be involved in mediating the renal elimination of sitagliptin. However, cyclosporine, a P-gp inhibitor, did not reduce the renal clearance of sitagliptin.

Specific Populations

Patients with Renal Impairment

An approximately 2-fold increase in the plasma AUC of sitagliptin was observed in patients with moderate renal impairment with eGFR of 30 to less than 45 mL/min/1.73 m^2, and an approximately 4-fold increase was observed in patients with severe renal impairment, including patients with ESRD on hemodialysis, as compared to normal healthy control subjects.

Patients with Hepatic Impairment

In patients with moderate hepatic impairment (Child-Pugh score 7 to 9), mean AUC and Cmax of sitagliptin increased approximately 21% and 13%, respectively, compared to healthy matched controls following administration of a single 100-mg dose of sitagliptin. These differences are not considered to be clinically meaningful.

There is no clinical experience in patients with severe hepatic impairment (Child-Pugh score >9).

Effects of Age, Body Mass Index (BMI), Gender, and Race

Based on a population pharmacokinetic analysis or a composite analysis of available pharmacokinetic data, BMI, gender, and race do not have a clinically meaningful effect on the pharmacokinetics of sitagliptin. When the effects of age on renal function are taken into account, age alone did not have a clinically meaningful impact on the pharmacokinetics of sitagliptin based on a population pharmacokinetic analysis. Elderly subjects (65 to 80 years) had approximately 19% higher plasma concentrations of sitagliptin compared to younger subjects.

Drug Interaction Studies

In Vitro Assessment of Drug Interactions

Sitagliptin is not an inhibitor of CYP isozymes CYP3A4, 2C8, 2C9, 2D6, 1A2, 2C19 or 2B6, and is not an inducer of CYP3A4. Sitagliptin is a P-gp substrate, but does not inhibit P-gp mediated transport of digoxin. Based on these results, sitagliptin is considered unlikely to cause interactions with other drugs that utilize these pathways.

Sitagliptin is not extensively bound to plasma proteins. Therefore, the propensity of sitagliptin to be involved in clinically meaningful drug-drug interactions mediated by plasma protein binding displacement is very low.

In Vivo Assessment of Drug Interactions

Effects of Sitagliptin on Other Drugs

In clinical studies, sitagliptin did not meaningfully alter the pharmacokinetics of metformin, glyburide, simvastatin, rosiglitazone, digoxin, warfarin, or an oral contraceptive (ethinyl estradiol and norethindrone) (Table 4), providing in vivo evidence of a low propensity for causing drug interactions with substrates of CYP3A4, CYP2C8, CYP2C9, P-gp, and organic cationic transporter (OCT).

Table 4: Effect of Sitagliptin on Systemic Exposure of Coadministered Drugs
Coadministered Drug | Dose of Coadministered Drug [All doses administered as single dose unless otherwise specified.] | Dose of Sitagliptin | Geometric Mean Ratio (ratio with/without sitagliptin) No Effect = 1
Coadministered Drug | Dose of Coadministered Drug [All doses administered as single dose unless otherwise specified.] | Dose of Sitagliptin |  | AUC [AUC is reported as AUC0-∞ unless otherwise specified.] | Cmax
Digoxin | 0.25 mg [Multiple dose.] once daily for 10 days | 100 mg once daily for 10 days | Digoxin | 1.11 [AUC0-24hr.] | 1.18
Glyburide | 1.25 mg | 200 mg once daily for 6 days | Glyburide | 1.09 | 1.01
Simvastatin | 20 mg | 200 mg once daily for 5 days | Simvastatin | 0.85 [AUC0-last.] | 0.80
Simvastatin | 20 mg | 200 mg once daily for 5 days | Simvastatin Acid | 1.12 | 1.06
Rosiglitazone | 4 mg | 200 mg once daily for 5 days | Rosiglitazone | 0.98 | 0.99
Warfarin | 30 mg single dose on day 5 | 200 mg once daily for 11 days | S(-) Warfarin | 0.95 | 0.89
Warfarin | 30 mg single dose on day 5 | 200 mg once daily for 11 days | R(+) Warfarin | 0.99 | 0.89
Ethinyl estradiol and norethindrone | 21 days once daily of 35 μg ethinyl estradiol with norethindrone 0.5 mg x 7 days, 0.75 mg x 7 days, 1 mg x 7 days | 200 mg once daily for 21 days | Ethinyl estradiol | 0.99 | 0.97
Ethinyl estradiol and norethindrone | 21 days once daily of 35 μg ethinyl estradiol with norethindrone 0.5 mg x 7 days, 0.75 mg x 7 days, 1 mg x 7 days | 200 mg once daily for 21 days | Norethindrone | 1.03 | 0.98
Metformin HCl | 1,000 mg twice daily for 14 days | 50 mg twice daily for 7 days | Metformin | 1.02 [AUC0-12hr.] | 0.97

Effects of Other Drugs on Sitagliptin

Clinical data described below suggest that sitagliptin is not susceptible to clinically meaningful interactions by coadministered medications (Table 5).

Table 5: Effect of Coadministered Drugs on Systemic Exposure of Sitagliptin
Coadministered Drug | Dose of Coadministered Drug [All doses administered as single dose unless otherwise specified.] | Dose of Sitagliptin | Geometric Mean Ratio (ratio with/without coadministered drugs) No Effect = 1
Coadministered Drug | Dose of Coadministered Drug [All doses administered as single dose unless otherwise specified.] | Dose of Sitagliptin |  | AUC [AUC is reported as AUC0-∞ unless otherwise specified.] | Cmax
Cyclosporine | 600 mg once daily | 100 mg once daily | Sitagliptin | 1.29 | 1.68
Metformin HCl | 1,000 mg [Multiple dose.] twice daily for 14 days | 50 mg‡ twice daily for 7 days | Sitagliptin | 1.02 [AUC0-12hr.] | 1.05

13 NONCLINICAL TOXICOLOGY

13.1 Carcinogenesis, Mutagenesis, Impairment of Fertility

A two-year carcinogenicity study was conducted in male and female rats given oral doses of sitagliptin of 50, 150, and 500 mg/kg/day. There was an increased incidence of combined liver adenoma/carcinoma in males and females and of liver carcinoma in females at 500 mg/kg. This dose results in exposures approximately 60 times the human exposure at the maximum recommended daily adult human dose (MRHD) of 100 mg/day based on AUC comparisons. Liver tumors were not observed at 150 mg/kg, approximately 20 times the human exposure at the MRHD. A two-year carcinogenicity study was conducted in male and female mice given oral doses of sitagliptin of 50, 125, 250, and 500 mg/kg/day. There was no increase in the incidence of tumors in any organ up to 500 mg/kg, approximately 70 times human exposure at the MRHD. Sitagliptin was not mutagenic or clastogenic with or without metabolic activation in the Ames bacterial mutagenicity assay, a Chinese hamster ovary (CHO) chromosome aberration assay, an in vitro cytogenetics assay in CHO, an in vitro rat hepatocyte DNA alkaline elution assay, and an in vivo micronucleus assay.

In rat fertility studies with oral gavage doses of 125, 250, and 1,000 mg/kg, males were treated for 4 weeks prior to mating, during mating, up to scheduled termination (approximately 8 weeks total) and females were treated 2 weeks prior to mating through gestation day 7. No adverse effect on fertility was observed at 125 mg/kg (approximately 12 times human exposure at the MRHD of 100 mg/day based on AUC comparisons). At higher doses, non-dose-related increased resorptions in females were observed (approximately 25 and 100 times human exposure at the MRHD based on AUC comparison).

14 CLINICAL STUDIES

There were approximately 5,200 patients with type 2 diabetes mellitus randomized in nine double-blind, placebo-controlled clinical safety and efficacy trials conducted to evaluate the effects of sitagliptin on glycemic control. In a pooled analysis of seven of these trials, the ethnic/racial distribution was approximately 59% White, 20% Hispanic or Latino ethnicity, 10% Asian, 6% Black or African American, and 6% other groups. Patients had an overall mean age of approximately 55 years (range 18 to 87 years). In addition, an active (glipizide)-controlled trial of 52-weeks duration was conducted in 1,172 patients with type 2 diabetes mellitus who had inadequate glycemic control on metformin.

In patients with type 2 diabetes mellitus, treatment with sitagliptin produced clinically significant improvements inA1C, fasting plasma glucose (FPG) and 2-hour post-prandial glucose (PPG) compared to placebo.

14.1 Monotherapy

A total of 1,262 patients with type 2 diabetes mellitus participated in two double-blind, placebo-controlled trials, one of 18-week and another of 24-week duration, to evaluate the efficacy and safety of sitagliptin monotherapy. In both monotherapy trials, patients currently on an antihyperglycemic agent discontinued the agent, and underwent a diet, exercise, and drug washout period of about 7 weeks. Patients with inadequate glycemic control (A1C 7% to 10%) after the washout period were randomized after completing a 2-week single-blind placebo run-in period; patients not currently on antihyperglycemic agents (off therapy for at least 8 weeks) with inadequate glycemic control (A1C 7% to 10%) were randomized after completing the 2-week single-blind placebo run-in period. In the 18-week trial, 521 patients were randomized to placebo, sitagliptin 100 mg, or sitagliptin 200 mg, and in the 24-week trial 741 patients were randomized to placebo, sitagliptin 100 mg, or sitagliptin 200 mg. Patients who failed to meet specific glycemic goals during the trials were treated with metformin rescue, added on to placebo or sitagliptin.

Treatment with sitagliptin at 100 mg daily provided significant improvements in A1C, FPG, and 2-hour PPG compared to placebo (Table 6). In the 18-week trial, 9% of patients receiving sitagliptin 100 mg and 17% who received placebo required rescue therapy. In the 24-week trial, 9% of patients receiving sitagliptin 100 mg and 21% of patients receiving placebo required rescue therapy. The improvement in A1C compared to placebo was not affected by gender, age, race, prior antihyperglycemic therapy, or baseline BMI. In these 18-and 24-week trials, among patients who were not on an antihyperglycemic agent at trial entry, the reductions from baseline in A1C were -0.7% and -0.8%, respectively, for those given sitagliptin, and -0.1% and -0.2%, respectively, for those given placebo. Overall, the 200 mg daily dose did not provide greater glycemic efficacy than the 100 mg daily dose. The effect of sitagliptin on lipid endpoints was similar to placebo. Body weight did not increase from baseline with sitagliptin therapy in either trial, compared to a small reduction in patients given placebo.

Table 6: Glycemic Parameters in 18- and 24-Week Placebo-Controlled Trials of Sitagliptin in Patients with Type 2 Diabetes Mellitus [Intent-to-treat population using last observation on trial prior to metformin rescue therapy.]
 | 18-Week Trial |  | 24-Week Trial
 | Sitagliptin 100 mg | Placebo | Sitagliptin 100 mg | Placebo
A1C (%) | N = 193 | N = 103 | N = 229 | N = 244
Baseline (mean) | 8 | 8.1 | 8 | 8
Change from baseline (adjusted mean [Least squares means adjusted for prior antihyperglycemic therapy status and baseline value.]) | -0.5 | 0.1 | -0.6 | 0.2
Difference from placebo (adjusted mean) (95% CI) | -0.6 [p<0.001 compared to placebo.] (-0.8, -0.4) |  | -0.8 (-1.0, -0.6)
Patients (%) achieving A1C <7% | 69 (36%) | 16 (16%) | 93 (41%) | 41 (17%)
FPG (mg/dL) | N = 201 | N = 107 | N = 234 | N = 247
Baseline (mean) | 180 | 184 | 170 | 176
Change from baseline (adjusted mean) | -13 | 7 | -12 | 5
Difference from placebo (adjusted mean) (95% CI) | -20 (-31, -9) |  | -17 (-24, -10)
2-hour PPG (mg/dL) | [Data not available.] |  | N = 201 | N = 204
Baseline (mean) |  |  | 257 | 271
Change from baseline (adjusted mean) |  |  | -49 | -2
Difference from placebo (adjusted mean) (95% CI) |  |  | -47 (-59, -34)

Additional Monotherapy Trial

A multinational, randomized, double-blind, placebo-controlled trial was also conducted to assess the safety and tolerability of sitagliptin in 91 patients with type 2 diabetes mellitus and chronic renal insufficiency (creatinine clearance <50 mL/min). Patients with moderate renal insufficiency received 50 mg daily of sitagliptin and those with severe renal insufficiency or with ESRD on hemodialysis or peritoneal dialysis received 25 mg daily. In this trial, the safety and tolerability of sitagliptin were generally similar to placebo. A small increase in serum creatinine was reported in patients with moderate renal insufficiency treated with sitagliptin relative to those on placebo. In addition, the reductions in A1C and FPG with sitagliptin compared to placebo were generally similar to those observed in other monotherapy trials. [see Clinical Pharmacology (12.3)].

14.2 Combination Therapy

Add-on Combination Therapy with Metformin

A total of 701 patients with type 2 diabetes mellitus participated in a 24-week, randomized, double-blind, placebo-controlled trial designed to assess the efficacy of sitagliptin in combination with metformin. Patients already on metformin HCl (N=431) at a dose of at least 1,500 mg per day were randomized after completing a 2-week single-blind placebo run-in period. Patients on metformin and another anti-hyperglycemic agent (N=229) and patients not on any antihyperglycemic agents (off therapy for at least 8 weeks, N=41) were randomized after a run-in period of approximately 10 weeks on metformin HCl (at a dose of at least 1,500 mg per day) in monotherapy. Patients with inadequate glycemic control (A1C 7% to 10%) were randomized to the addition of either 100 mg of sitagliptin or placebo, administered once daily. Patients who failed to meet specific glycemic goals during the trials were treated with pioglitazone rescue.

In combination with metformin, sitagliptin provided significant improvements in A1C, FPG, and 2-hour PPG compared to placebo with metformin (Table 7). Rescue glycemic therapy was used in 5% of patients treated with sitagliptin 100 mg and 14% of patients treated with placebo. A similar decrease in body weight was observed for both treatment groups.

Table 7: Glycemic Parameters at Final Visit (24-Week Trial) for Sitagliptin in Add-on Combination Therapy with Metformin [Intent-to-treat population using last observation on trial prior to pioglitazone rescue therapy.]
 | Sitagliptin 100 mg + Metformin | Placebo + Metformin
A1C (%) | N = 453 | N = 224
Baseline (mean) | 8 | 8
Change from baseline (adjusted mean [Least squares means adjusted for prior antihyperglycemic therapy and baseline value.]) | -0.7 | -0
Difference from placebo + metformin (adjusted mean) (95% CI) | -0.7 [p<0.001 compared to placebo + metformin.] (-0.8, -0.5)
Patients (%) achieving A1C <7% | 213 (47%) | 41 (18%)
FPG (mg/dL) | N = 454 | N = 226
Baseline (mean) | 170 | 174
Change from baseline (adjusted mean) | -17 | 9
Difference from placebo + metformin (adjusted mean) (95% CI) | -25 (-31, -20)
2-hour PPG (mg/dL) | N = 387 | N = 182
Baseline (mean) | 275 | 272
Change from baseline (adjusted mean) | -62 | -11
Difference from placebo + metformin (adjusted mean) (95% CI) | -51 (-61, -41)

Initial Combination Therapy with Metformin

A total of 1,091 patients with type 2 diabetes mellitus and inadequate glycemic control on diet and exercise participated in a 24-week, randomized, double-blind, placebo-controlled factorial trial designed to assess the efficacy of sitagliptin as initial therapy in combination with metformin. Patients on an antihyperglycemic agent (N=541) discontinued the agent, and underwent a diet, exercise, and drug washout period of up to 12 weeks duration. After the washout period, patients with inadequate glycemic control (A1C 7.5% to 11%) were randomized after completing a 2-week single-blind placebo run-in period. Patients not on antihyperglycemic agents at trial entry (N=550) with inadequate glycemic control (A1C 7.5% to 11%) immediately entered the 2-week single-blind placebo run-in period and then were randomized. Approximately equal numbers of patients were randomized to receive initial therapy with placebo, 100 mg of sitagliptin once daily, 500 mg or 1,000 mg of metformin HCl twice daily, or 50 mg of sitagliptin twice daily in combination with 500 mg or 1,000 mg of metformin HCl twice daily. Patients who failed to meet specific glycemic goals during the trial were treated with glyburide (glibenclamide) rescue.

Initial therapy with the combination of sitagliptin and metformin provided significant improvements in A1C, FPG, and 2-hour PPG compared to placebo, to metformin alone, and to sitagliptin alone (Table 8, Figure 1). Mean reductions from baseline in A1C were generally greater for patients with higher baseline A1C values. For patients not on an antihyperglycemic agent at trial entry, mean reductions from baseline in A1C were: sitagliptin 100 mg once daily, -1.1%; metformin HCl 500 mg bid, -1.1%; metformin HCl 1,000 mg bid, -1.2%; sitagliptin 50 mg bid with metformin HCl 500 mg bid, -1.6%; sitagliptin 50 mg bid with metformin HCl 1,000 mg bid, -1.9%; and for patients receiving placebo, -0.2%. Lipid effects were generally neutral. The decrease in body weight in the groups given sitagliptin in combination with metformin was similar to that in the groups given metformin alone or placebo.

Table 8: Glycemic Parameters at Final Visit (24-Week Trial) for Sitagliptin and Metformin, Alone and in Combination as Initial Therapy [Intent-to-treat population using last observation on trial prior to glyburide (glibenclamide) rescue therapy.]
 | Placebo | Sitagliptin 100 mg QD | Metformin HCl 500 mg bid | Metformin HCl 1,000 mg bid | Sitagliptin 50 mg bid + Metformin HCl 500 mg bid | Sitagliptin 50 mg bid + Metformin HCl 1,000 mg bid
A1C (%) | N = 165 | N = 175 | N = 178 | N = 177 | N = 183 | N = 178
Baseline (mean) | 8.7 | 8.9 | 8.9 | 8.7 | 8.8 | 8.8
Change from baseline (adjusted mean [Least squares means adjusted for prior antihyperglycemic therapy status and baseline value.]) | 0.2 | -0.7 | -0.8 | -1.1 | -1.4 | -1.9
Difference from placebo (adjusted mean) (95% CI) |  | -0.8 [p<0.001 compared to placebo.] (-1.1, -0.6) | -1 (-1.2, -0.8) | -1.3 (-1.5, -1.1) | -1.6 (-1.8, -1.3) | -2.1 (-2.3, -1.8)
Patients (%) achieving A1C <7% | 15 (9%) | 35 (20%) | 41 (23%) | 68 (38%) | 79 (43%) | 118 (66%)
% Patients receiving rescue medication | 32 | 21 | 17 | 12 | 8 | 2
FPG (mg/dL) | N = 169 | N = 178 | N = 179 | N = 179 | N = 183 | N = 180
Baseline (mean) | 196 | 201 | 205 | 197 | 204 | 197
Change from baseline (adjusted mean) | 6 | -17 | -27 | -29 | -47 | -64
Difference from placebo (adjusted mean) (95% CI) |  | -23 (-33, -14) | -33 (-43, -24) | -35 (-45, -26) | -53 (-62, -43) | -70 (-79, -60)
2-hour PPG (mg/dL) | N = 129 | N = 136 | N = 141 | N = 138 | N = 147 | N = 152
Baseline (mean) | 277 | 285 | 293 | 283 | 292 | 287
Change from baseline (adjusted mean) | 0 | -52 | -53 | -78 | -93 | -117
Difference from placebo (adjusted mean) (95% CI) |  | -52 (-67, -37) | -54 (-69, -39) | -78 (-93, -63) | -93 (-107, -78) | -117 (-131, -102)

Figure 1: Mean Change from Baseline for A1C (%) over 24 Weeks with Sitagliptin and Metformin, Alone and in Combination as Initial Therapy in Patients with Type 2 Diabetes Mellitus*

*All Patients Treated Population: least squares means adjusted for prior antihyperglycemic therapy and baseline value.

Initial combination therapy or maintenance of combination therapy may not be appropriate for all patients. These management options are left to the discretion of the health care provider.

Active-Controlled Trial vs Glipizide in Combination with Metformin

The efficacy of sitagliptin was evaluated in a 52-week, double-blind, glipizide-controlled noninferiority trial in patients with type 2 diabetes mellitus. Patients not on treatment or on other antihyperglycemic agents entered a run-in treatment period of up to 12 weeks duration with metformin HCl monotherapy (dose of ≥1,500 mg per day) which included washout of medications other than metformin, if applicable. After the run-in period, those with inadequate glycemic control (A1C 6.5% to 10%) were randomized 1:1 to the addition of sitagliptin 100 mg once daily or glipizide for 52 weeks. Patients receiving glipizide were given an initial dosage of 5 mg/day and then electively titrated over the next 18 weeks to a maximum dosage of 20 mg/day as needed to optimize glycemic control. Thereafter, the glipizide dose was to be kept constant, except for down-titration to prevent hypoglycemia. The mean dose of glipizide after the titration period was 10 mg.

After 52 weeks, sitagliptin and glipizide had similar mean reductions from baseline in A1C in the intent-to-treat analysis (Table 9). These results were consistent with the per protocol analysis (Figure 2). A conclusion in favor of the non-inferiority of sitagliptin to glipizide may be limited to patients with baseline A1C comparable to those included in the trial (over 70% of patients had baseline A1C <8% and over 90% had A1C <9%).

Table 9: Glycemic Parameters in a 52-Week Trial Comparing Sitagliptin to Glipizide as Add-On Therapy in Patients Inadequately Controlled on Metformin (Intent-to-Treat Population) [The intent-to-treat analysis used the patients' last observation in the trial prior to discontinuation.]
 | Sitagliptin 100 mg | Glipizide
A1C (%) | N = 576 | N = 559
Baseline (mean) | 7.7 | 7.6
Change from baseline (adjusted mean [Least squares means adjusted for prior antihyperglycemic therapy status and baseline A1C value.]) | -0.5 | -0.6
FPG (mg/dL) | N = 583 | N = 568
Baseline (mean) | 166 | 164
Change from baseline (adjusted mean) | -8 | -8

Figure 2: Mean Change from Baseline for A1C (%) Over 52 Weeks in a Trial Comparing Sitagliptin to Glipizide as Add-On Therapy in Patients Inadequately Controlled on Metformin (Per Protocol Population)*

■ Sitagliptin 100 mg ○ Glipizide

*The per protocol population (mean baseline A1C of 7.5%) included patients without major protocol violations who had observations at baseline and at Week 52.

The incidence of hypoglycemia in the Sitagliptin group (4.9%) was significantly (p<0.001) lower than that in the glipizide group (32%). Patients treated with Sitagliptin exhibited a significant mean decrease from baseline in body weight compared to a significant weight gain in patients administered glipizide (-1.5 kg vs +1.1 kg).

Add-on Combination Therapy with Pioglitazone

A total of 353 patients with type 2 diabetes mellitus participated in a 24-week, randomized, double-blind, placebo-controlled trial designed to assess the efficacy of sitagliptin in combination with pioglitazone. Patients on any oral antihyperglycemic agent in monotherapy (N=212) or on a PPARγ agent in combination therapy (N=106) or not on an antihyperglycemic agent (off therapy for at least 8 weeks, N=34) were switched to monotherapy with pioglitazone (at a dose of 30 to 45 mg per day) and completed a run-in period of approximately 12 weeks in duration. After the run-in period on pioglitazone monotherapy, patients with inadequate glycemic control (A1C 7% to 10%) were randomized to the addition of either 100 mg of sitagliptin or placebo, administered once daily. Patients who failed to meet specific glycemic goals during the trials were treated with metformin rescue. Glycemic endpoints measured were A1C and fasting glucose.

In combination with pioglitazone, sitagliptin provided significant improvements in A1C and FPG compared to placebo with pioglitazone (Table 10). Rescue therapy was used in 7% of patients treated with sitagliptin 100 mg and 14% of patients treated with placebo. There was no significant difference between sitagliptin and placebo in body weight change.

Table 10: Glycemic Parameters at Final Visit (24-Week Trial) for Sitagliptin in Add-on Combination Therapy with Pioglitazone [Intent-to-treat population using last observation on trial prior to metformin rescue therapy.]
 | Sitagliptin 100 mg + Pioglitazone | Placebo + Pioglitazone
A1C (%) | N = 163 | N = 174
Baseline (mean) | 8.1 | 8.0
Change from baseline (adjusted mean [Least squares means adjusted for prior antihyperglycemic therapy status and baseline value.]) | -0.9 | -0.2
Difference from placebo + pioglitazone (adjusted mean) (95% CI) | -0.7 [p<0.001 compared to placebo + pioglitazone.] (-0.9, -0.5)
Patients (%) achieving A1C <7% | 74 (45%) | 40 (23%)
FPG (mg/dL) | N = 163 | N = 174
Baseline (mean) | 168 | 166
Change from baseline (adjusted mean) | -17 | 1
Difference from placebo + pioglitazone (adjusted mean) (95% CI) | -18 (-24, -11)

Initial Combination Therapy with Pioglitazone

A total of 520 patients with type 2 diabetes mellitus and inadequate glycemic control on diet and exercise participated in a 24-week, randomized, double-blind trial designed to assess the efficacy of sitagliptin as initial therapy in combination with pioglitazone. Patients not on antihyperglycemic agents at trial entry (<4 weeks cumulative therapy over the past 2 years, and with no treatment over the prior 4 months) with inadequate glycemic control (A1C 8% to 12%) immediately entered the 2-week single-blind placebo run-in period and then were randomized. Approximately equal numbers of patients were randomized to receive initial therapy with 100 mg of sitagliptin in combination with 30 mg of pioglitazone once daily or 30 mg of pioglitazone once daily as monotherapy. There was no glycemic rescue therapy in this trial.

Initial therapy with the combination of sitagliptin and pioglitazone provided significant improvements in A1C, FPG, and 2-hour PPG compared to pioglitazone monotherapy (Table 11). The improvement in A1C was generally consistent across subgroups defined by gender, age, race, baseline BMI, baseline A1C, or duration of disease. In this trial, patients treated with ZITUVIO in combination with pioglitazone had a mean increase in body weight of 1.1 kg compared to pioglitazone alone (3 kg vs. 1.9 kg). Lipid effects were generally neutral.

Table 11: Glycemic Parameters at Final Visit (24-Week Trial) for Sitagliptin in Combination with Pioglitazone as Initial Therapy [Intent-to-treat population using last observation on trial.]
 | Sitagliptin 100 mg + Pioglitazone | Pioglitazone
A1C (%) | N = 251 | N = 246
Baseline (mean) | 9.5 | 9.4
Change from baseline (adjusted mean [Least squares means adjusted for baseline value.]) | -2.4 | -1.5
Difference from pioglitazone (adjusted mean) (95% CI) | -0.9 [p<0.001 compared to placebo + pioglitazone.] (-1.1, -0.7)
Patients (%) achieving A1C <7% | 151 (60%) | 68 (28%)
FPG (mg/dL) | N = 256 | N = 253
Baseline (mean) | 203 | 201
Change from baseline (adjusted mean) | -63 | -40
Difference from pioglitazone (adjusted mean) (95% CI) | -23 (-30, -15)
2-hour PPG (mg/dL) | N = 216 | N = 211
Baseline (mean) | 283 | 284
Change from baseline (adjusted mean) | -114 | -69
Difference from pioglitazone (adjusted mean) (95% CI) | -45 (-57, -32)

Add-on Combination Therapy with Metformin and Rosiglitazone

A total of 278 patients with type 2 diabetes mellitus participated in a 54-week, randomized, double-blind, placebo-controlled trial designed to assess the efficacy of sitagliptin in combination with metformin and rosiglitazone. Patients on dual therapy with metformin HCl ≥1,500 mg/day and rosiglitazone ≥4 mg/day or with metformin HCl ≥1,500 mg/day and pioglitazone ≥30 mg/day (switched to rosiglitazone ≥4 mg/day) entered a dose-stable run-in period of 6 weeks. Patients on other dual therapy were switched to metformin HCl ≥1,500 mg/day and rosiglitazone ≥4 mg/day in a dose titration/stabilization run-in period of up to 20 weeks in duration. After the run-in period, patients with inadequate glycemic control (A1C 7.5% to 11%) were randomized 2:1 to the addition of either 100 mg of sitagliptin or placebo, administered once daily. Patients who failed to meet specific glycemic goals during the trial were treated with glipizide (or other sulfonylurea) rescue. The primary time point for evaluation of glycemic parameters was Week 18.

In combination with metformin and rosiglitazone, sitagliptin provided significant improvements in A1C, FPG, and 2-hour PPG compared to placebo with metformin and rosiglitazone (Table 12) at Week 18. At Week 54, mean reduction in A1C was -1.0% for patients treated with sitagliptin and -0.3% for patients treated with placebo in an analysis based on the intent-to-treat population. Rescue therapy was used in 18% of patients treated with sitagliptin 100 mg and 40% of patients treated with placebo. There was no significant difference between sitagliptin and placebo in body weight change.

Table 12: Glycemic Parameters at Week 18 for Sitagliptin in Add-on Combination Therapy with Metformin and Rosiglitazone [Intent-to-treat population using last observation on trial prior to glipizide (or other sulfonylurea) rescue therapy.]
 | Sitagliptin 100 mg + Metformin + Rosiglitazone | Placebo + Metformin + Rosiglitazone
A1C (%) | N = 176 | N = 93
Baseline (mean) | 8.8 | 8.7
Change from baseline (adjusted mean [Least squares means adjusted for prior antihyperglycemic therapy status and baseline value.]) | -1 | -0.4
Difference from placebo + rosiglitazone + metformin (adjusted mean) (95% CI) | -0.7 [p<0.001 compared to placebo + metformin + rosiglitazone.] (-0.9, -0.4)
Patients (%) achieving A1C <7% | 39 (22%) | 9 (10%)
FPG (mg/dL) | N = 179 | N = 94
Baseline (mean) | 181 | 182
Change from baseline (adjusted mean) | -30 | -11
Difference from placebo + rosiglitazone + metformin (adjusted mean) (95% CI) | -18 (-26, -10)
2-hour PPG (mg/dL) | N = 152 | N = 80
Baseline (mean) | 256 | 248
Change from baseline (adjusted mean) | -59 | -21
Difference from placebo + rosiglitazone + metformin (adjusted mean) (95% CI) | -39 (-51, -26)

Add-on Combination Therapy with Glimepiride, with or without Metformin

A total of 441 patients with type 2 diabetes mellitus participated in a 24-week, randomized, double-blind, placebo-controlled trial designed to assess the efficacy of sitagliptin in combination with glimepiride, with or without metformin. Patients entered a run-in treatment period on glimepiride (≥4 mg per day) alone or glimepiride in combination with metformin HCl (≥1,500 mg per day). After a dose-titration and dose-stable run-in period of up to 16 weeks and a 2-week placebo run-in period, patients with inadequate glycemic control (A1C 7.5% to 10.5%) were randomized to the addition of either 100 mg of sitagliptin or placebo, administered once daily. Patients who failed to meet specific glycemic goals during the trials were treated with pioglitazone rescue.

In combination with glimepiride, with or without metformin, sitagliptin provided significant improvements in A1C and FPG compared to placebo (Table 13). In the entire trial population (patients on sitagliptin in combination with glimepiride and patients on sitagliptin in combination with glimepiride and metformin), a mean reduction from baseline relative to placebo in A1C of -0.7% and in FPG of -20 mg/dL was seen. Rescue therapy was used in 12% of patients treated with sitagliptin 100 mg and 27% of patients treated with placebo. In this trial, patients treated with sitagliptin had a mean increase in body weight of 1.1 kg vs. placebo (+0.8 kg vs. -0.4 kg). In addition, there was an increased rate of hypoglycemia. [see Warnings and Precautions (5.4) and Adverse Reactions (6.1) ].

Table 13: Glycemic Parameters at Final Visit (24-Week Trial) for Sitagliptin as Add-On Combination Therapy with Glimepiride, with or without Metformin [Intent-to-treat population using last observation on trial prior to pioglitazone rescue therapy.]
 | Sitagliptin 100 mg + Glimepiride | Placebo + Glimepiride | Sitagliptin 100 mg + Glimepiride + Metformin | Placebo + Glimepiride + Metformin
A1C (%) | N = 102 | N = 103 | N = 115 | N = 105
Baseline (mean) | 8.4 | 8.5 | 8.3 | 8.3
Change from baseline (adjusted mean [Least squares means adjusted for prior antihyperglycemic therapy status and baseline value.]) | -0.3 | 0.3 | -0.6 | 0.3
Difference from placebo (adjusted mean) (95% CI) | -0.6 [p<0.001 compared to placebo.] (-0.8, -0.3) |  | -0.9 (-1.1, -0.7)
Patients (%) achieving A1C <7% | 11 (11%) | 9 (9%) | 26 (23%) | 1 (1%)
FPG (mg/dL) | N = 104 | N = 104 | N = 115 | N = 109
Baseline (mean) | 183 | 185 | 179 | 179
Change from baseline (adjusted mean) | -1 | 18 | -8 | 13
Difference from placebo (adjusted mean) (95% CI) | -19 [p<0.01 compared to placebo.] (-32, -7) |  | -21 (-32, -10)

Add-on Combination Therapy with Insulin (with or without Metformin)

A total of 641 patients with type 2 diabetes mellitus participated in a 24-week, randomized, double-blind, placebo-controlled trial designed to assess the efficacy of sitagliptin as add-on to insulin therapy (with or without metformin). The racial distribution in this trial was approximately 70% White, 18% Asian, 7% Black or African American, and 5% other groups. Approximately 14% of the patients in this trial were Hispanic or Latino. Patients entered a 2-week, single-blind run-in treatment period on pre-mixed, long-acting, or intermediate-acting insulin, with or without metformin HCl (≥1,500 mg per day). Patients using short-acting insulins were excluded unless the short-acting insulin was administered as part of a pre-mixed insulin. After the run-in period, patients with inadequate glycemic control (A1C 7.5% to 11%) were randomized to the addition of either 100 mg of ZITUVIO or placebo, administered once daily. Patients were on a stable dose of insulin prior to enrolment with no changes in insulin dose permitted during the run-in period. Patients who failed to meet specific glycemic goals during the double-blind treatment period were to have up-titration of the background insulin dose as rescue therapy.

The median daily insulin dose at baseline was 42 units in the patients treated with sitagliptin and 45 units in the placebo-treated patients. The median change from baseline in daily dose of insulin was zero for both groups at the end of the trial. In combination with insulin (with or without metformin), sitagliptin provided significant improvements in A1C, FPG, and 2-hour PPG compared to placebo (Table 14). Both treatment groups had an adjusted mean increase in body weight of 0.1 kg from baseline to Week 24. There was an increased rate of hypoglycemia in patients treated with sitagliptin. [see Warnings and Precautions (5.4) and Adverse Reactions (6.1)].

Table 14: Glycemic Parameters at Final Visit (24-Week Trial) for Sitagliptin as Add-on Combination Therapy with Insulin [Intent-to-treat population using last observation on trial prior to rescue therapy.]
 | Sitagliptin 100 mg + Insulin (+/- Metformin) | Placebo + Insulin (+/- Metformin)
A1C (%) | N = 305 | N = 312
Baseline (mean) | 8.7 | 8.6
Change from baseline (adjusted mean [Least squares means adjusted for metformin use at the screening visit (yes/no), type of insulin used at the screening visit (pre-mixed vs. non-pre-mixed [intermediate-or long-acting]), and baseline value.]) | -0.6 | -0.1
Difference from placebo (adjusted mean, [Treatment by stratum interaction was not significant (p>0.10) for metformin stratum and for insulin stratum.]) (95% CI) | -0.6 [p<0.001 compared to placebo.] (-0.7, -0.4)
Patients (%) achieving A1C <7% | 39 (12.8%) | 16 (5.1%)
FPG (mg/dL) | N = 310 | N = 313
Baseline (mean) | 176 | 179
Change from baseline (adjusted mean) | -18 | -4
Difference from placebo (adjusted mean) (95% CI) | -15 (-23, -7)
2-hour PPG (mg/dL) | N = 240 | N = 257
Baseline (mean) | 291 | 292
Change from baseline (adjusted mean) | -31 | 5
Difference from placebo (adjusted mean) (95% CI) | -36 (-47, -25)

Maintenance of Sitagliptin During Initiation and Titration of Insulin Glargine

A total of 746 patients with type 2 diabetes mellitus (mean baseline HbA1C 8.8%, disease duration 10.8 years) participated in a 30-week, randomized, double-blind, placebo-controlled trial to assess the efficacy and safety of continuing sitagliptin during the initiation and uptitration of insulin glargine. Patients who were on a stable dose of metformin (≥1,500 mg/day) in combination with a DPP-4 inhibitor and/or sulfonylurea but with inadequate glycemic control (A1C 7.5% to 11%) were enrolled in the trial. Those on metformin and sitagliptin (100 mg/day) directly entered the double-blind treatment period; those on another DPP-4 inhibitor and/or on a sulfonylurea entered a 4 to 8 week run-in period in which they were maintained on metformin and switched to sitagliptin (100 mg); other DPP-4 inhibitors and sulfonylureas were discontinued. At randomization patients were randomized either to continue sitagliptin or to discontinue sitagliptin and switch to a matching placebo. On the day of randomization, insulin glargine was initiated at a dose of 10 units subcutaneously in the evening. Patients were instructed to up-titrate their insulin dose in the evening based on fasting blood glucose measurements to achieve a target of 72 to 100 mg/dL.

At 30 weeks, the mean reduction in A1C was greater in the sitagliptin group than in the placebo group (Table 15). At the end of the trial, 27.3% of patients in the sitagliptin group and 27.3% in the placebo group had a fasting plasma glucose (FPG) in the target range; there was no significant difference in insulin dose between arms.

Table 15: Change from Baseline in A1C and FPG at Week 30 in the Maintenance of Sitagliptin During Initiation and Titration of Insulin Glargine Trial
 | Sitagliptin 100 mg +Metformin + Insulin Glargine | Placebo +Metformin + Insulin Glargine
A1C (%) | N = 373 [N is the number of randomized and treated patients.] | N = 370
Baseline (mean) | 8.8 | 8.8
Week 30 (mean) | 6.9 | 7.3
Change from baseline (adjusted mean) [Analysis of Covariance including all post-baseline data regardless of rescue or treatment discontinuation. Model estimates calculated using multiple imputation to model washout of the treatment effect using placebo data for all subjects having missing Week 30 data.] | -1.9 | -1.4
Difference from placebo (adjusted mean) (95% CI) | -0.4 (-0.6, -0.3) [p<0.001 compared to placebo.]
Patients (%) with A1C <7% | 202 (54.2%) | 131 (35.4%)
FPG (mg/dL) | N = 373 | N = 370
Baseline (mean) | 199 | 201
Week 30 (mean) | 118 | 123
Change from baseline (adjusted mean) | -81 | -76

16 HOW SUPPLIED/STORAGE AND HANDLING

ZITUVIO are supplied as follows:
Tablet Strength | Physical Description | How Supplied | NDC #
25 mg sitagliptin | White to off white, round, biconvex, film coated tablets debossed with "12" on one side and "40" on the other side | Bottles of 30 tablets with child-resistant closure. | NDC 70771-1770-3
25 mg sitagliptin | White to off white, round, biconvex, film coated tablets debossed with "12" on one side and "40" on the other side | Bottles of 90 tablets with child-resistant closure. | NDC 70771-1770-9
25 mg sitagliptin | White to off white, round, biconvex, film coated tablets debossed with "12" on one side and "40" on the other side | Bottles of 1,000 tablets | NDC 70771-1770-0
50 mg sitagliptin | Pale yellow, round, biconvex, film coated tablets debossed with "12" on one side and "41" on the other side | Bottles of 30 tablets with child-resistant closure. | NDC 70771-1771-3
50 mg sitagliptin | Pale yellow, round, biconvex, film coated tablets debossed with "12" on one side and "41" on the other side | Bottles of 90 tablets with child-resistant closure. | NDC 70771-1771-9
50 mg sitagliptin | Pale yellow, round, biconvex, film coated tablets debossed with "12" on one side and "41" on the other side | Bottles of 1,000 tablets | NDC 70771-1771-0
100 mg sitagliptin | Beige, round, biconvex, film coated tablets debossed with "12" on one side and "42" on the other side | Bottles of 30 tablets with child-resistant closure. | NDC 70771-1772-3
100 mg sitagliptin | Beige, round, biconvex, film coated tablets debossed with "12" on one side and "42" on the other side | Bottles of 90 tablets with child-resistant closure. | NDC 70771-1772-9
100 mg sitagliptin | Beige, round, biconvex, film coated tablets debossed with "12" on one side and "42" on the other side | Bottles of 1,000 tablets | NDC 70771-1772-0

Storage

Store at 20°C to 25°C (68°F to 77°F), excursions permitted between 15°C and 30°C (59°F and 86°F), [see USP Controlled Room Temperature].

Protect from moisture.

Once the bottle has been opened, the product must be used within 6 months.

17 PATIENT COUNSELING INFORMATION

Advise the patient to read the FDA-approved patient labeling (Medication Guide).

Pancreatitis

Inform patients that acute pancreatitis has been reported during postmarketing use of sitagliptin. Inform patients that persistent severe abdominal pain, sometimes radiating to the back, which may or may not be accompanied by vomiting, is the hallmark symptom of acute pancreatitis. Instruct patients to promptly discontinue ZITUVIO and contact their physician if persistent severe abdominal pain occurs [see Warnings and Precautions (5.1)].

Heart Failure

Inform patients of the signs and symptoms of heart failure. Before initiating ZITUVIO, ask patients about a history of heart failure or other risk factors for heart failure including moderate to severe renal impairment. Instruct patients to contact their health care provider as soon as possible if they experience symptoms of heart failure, including increasing shortness of breath, rapid increase in weight or swelling of the feet [see Warnings and Precautions (5.2)].

Hypoglycemia

Inform patients that the incidence of hypoglycemia is increased when sitagliptin is added to a sulfonylurea or insulin. Explain to patients receiving ZITUVIO in combination with these medications the risks of hypoglycemia, its symptoms and treatment, and conditions that predispose to its development [see Warnings and Precautions (5.4)].

Hypersensitivity Reactions

Inform patients that allergic reactions have been reported during postmarketing use of sitagliptin. If symptoms of allergic reactions (including rash, hives, and swelling of the face, lips, tongue, and throat that may cause difficulty in breathing or swallowing) occur, patients must stop taking ZITUVIO and seek medical advice promptly. [see Warnings and Precautions (5.5)].

Severe and Disabling Arthralgia

Inform patients that severe and disabling joint pain may occur with this class of drugs. The time to onset of symptoms can range from one day to years. Instruct patients to seek medical advice if severe joint pain occurs [see Warnings and Precautions (5.6)].

Bullous Pemphigoid

Inform patients that bullous pemphigoid may occur with this class of drugs. Instruct patients to seek medical advice if blisters or erosions occur [see Warnings and Precautions (5.7)].

Medication Guide available at www.zydususa.com/medguides/ or call 1-877-993-8779

Manufactured by:

Zydus Lifesciences Ltd.,

Pharmez, Matoda, Ahmedabad, India.

MEDICATION GUIDE

ZITUVIO® (zi too' vee oh)
(sitagliptin)
tablets, for oral use

What is the most important information I should know about ZITUVIO ?
ZITUVIO can cause serious side effects, including:
Inflammation of the pancreas (pancreatitis) which may be severe and lead to death . Certain medical problems make you more likely to get pancreatitis.
Before you start taking ZITUVIO , tell your healthcare provider if you have ever had:
o pancreatitis
o stones in your gallbladder (gallstones)
o high blood triglyceride levels
o a history of alcoholism
o kidney problems
Stop taking ZITUVIO and call your healthcare provider right away if you have pain in your stomach area (abdomen) that is severe and will not go away. The pain may be felt going from your abdomen through to your back. The pain may happen with or without vomiting. These may be symptoms of pancreatitis.
Heart failure . Heart failure means your heart does not pump blood well enough.
Before you start taking ZITUVIO , tell your healthcare provider if you have ever had heart failure or have problems with your kidneys. Contact your healthcare provider right away if you have any of the following symptoms:
o increasing shortness of breath or trouble breathing, especially when you lie down
o swelling or fluid retention, especially in the feet, ankles, or legs
o an unusually fast increase in weight
o unusual tiredness
These may be symptoms of heart failure.

What is ZITUVIO ?
ZITUVIO is a prescription medicine used along with diet and exercise to lower blood sugar in adults with type 2 diabetes.
ZITUVIO is not for people with type 1 diabetes.
If you have had pancreatitis (inflammation of the pancreas) in the past, it is not known if you have a higher chance of getting pancreatitis while you take ZITUVIO.
It is not known if ZITUVIO is safe and effective in children.

Do not take ZITUVIO if:
you are allergic to sitagliptin or any of the ingredients in ZITUVIO. See the end of this Medication Guide for a complete list of ingredients in ZITUVIO.
Symptoms of a serious allergic reaction to ZITUVIO may include rash, raised red patches on your skin (hives), or swelling of the face, lips, tongue, and throat that may cause difficulty breathing or swallowing.

Before you take ZITUVIO, tell your healthcare provider about all of your medical conditions, including if you:
have or have had inflammation of your pancreas (pancreatitis).
have kidney problems.
have heart failure.
are pregnant or plan to become pregnant. It is not known if ZITUVIO will harm your unborn baby. If you are pregnant, talk with your healthcare provider about the best way to control your blood sugar while you are pregnant.
are breastfeeding or plan to breastfeed. It is not known if ZITUVIO will pass into your breast milk. Talk with your healthcare provider about the best way to feed your baby if you are taking ZITUVIO.
Tell your healthcare provider about all the medicines you take , including prescription and over-the-counter medicines, vitamins, and herbal supplements.
Know the medicines you take. Keep a list of your medicines and show it to your healthcare provider and pharmacist when you get a new medicine.

How should I take ZITUVIO ?
Take ZITUVIO 1 time each day exactly as your healthcare provider tells you.
You can take ZITUVIO with or without food.
Your healthcare provider will do blood tests to check how well your kidneys are working before and during your treatment with ZITUVIO.
Your healthcare provider may tell you to take ZITUVIO along with other diabetes medicines. Low blood sugar can happen more often when ZITUVIO is taken with certain other diabetes medicines. See " What are the possible side effects of ZITUVIO? ".
If you take too much ZITUVIO, call your healthcare provider or the Poison Help Line at 1-800-222-1222 or go to the nearest hospital emergency room right away.

What are the possible side effects of ZITUVIO?
ZITUVIO may cause serious side effects, including:
See "What is the most important information I should know about ZITUVIO?" .
Kidney problems , sometimes requiring dialysis.
Low blood sugar (hypoglycemia). If you take ZITUVIO with another medicine that can cause low blood sugar, such as a sulfonylurea or insulin, your risk of getting low blood sugar is higher. The dose of your sulfonylurea medicine or insulin may need to be lowered while you use ZITUVIO. Signs and symptoms of low blood sugar may include:

o headache
o drowsiness
o irritability
o hunger
o dizziness

o confusion
o sweating
o feeling jittery
o weakness
o fast heartbeat

Serious allergic reactions. If you have any symptoms of a serious allergic reaction, stop taking ZITUVIO and call your healthcare provider right away or get emergency medical help. See " Do not take ZITUVIO if: ". Your healthcare provider may give you a medicine for your allergic reaction and prescribe a different medicine for your diabetes.
Joint pain. Some people who take ZITUVIO, may develop joint pain that can be severe. Call your healthcare provider if you have severe joint pain.
Skin reaction. Some people who take ZITUVIO may develop a skin reaction called bullous pemphigoid that can require treatment in a hospital. Tell your healthcare provider right away if you develop blisters or the breakdown of the outer layer of your skin (erosion). Your healthcare provider may tell you to stop taking ZITUVIO.
The most common side effects of ZITUVIO include upper respiratory infection, stuffy or runny nose and sore throat, and headache.
These are not all the possible side effects of ZITUVIO. For more information, ask your healthcare provider or pharmacist.
Tell your healthcare provider if you have any side effect that bothers you or does not go away. Call your doctor for medical advice about side effects. You may report side effects to FDA at 1-800-FDA-1088.

How should I store ZITUVIO?
Store ZITUVIO at room temperature between 68°F to 77°F (20°C to 25°C).
Protect it from moisture
Use ZITUVIO within 6 months of opening the bottle
Keep ZITUVIO and all medicines out of the reach of children.

General information about the safe and effective use of ZITUVIO
Medicines are sometimes prescribed for purposes other than those listed in a Medication Guide. Do not use ZITUVIO for a condition for which it was not prescribed. Do not give ZITUVIO to other people, even if they have the same symptoms you have. It may harm them.
You can ask your pharmacist or healthcare provider for information about ZITUVIO that is written for health professionals.

What are the ingredients in ZITUVIO?
Active ingredient: sitagliptin
Inactive ingredients: anhydrous dibasic calcium phosphate, colloidal silicon dioxide, croscarmellose sodium, malic acid, magnesium stearate, microcrystalline cellulose, and povidone. In addition, the film coating contains the following inactive ingredients: polyethylene glycol, polyvinyl alcohol, talc, and titanium dioxide. The 50 mg tablet's film coating also contains ferrosoferric oxide and iron oxide yellow. The 100 mg tablet's film coating also contains FD&C Yellow #6 Aluminum Lake and iron oxide yellow.
Manufactured by: Zydus Lifesciences Ltd., Pharmez, Matoda, Ahmedabad, India
The trademarks depicted herein are owned by their respective companies.
Please address medical inquiries to, (MedicalAffairs@zydususa.com) 1-877-993-8779.

This Medication Guide has been approved by the U.S. Food and Drug Administration Revised: 01/25

PACKAGE LABEL.PRINCIPAL DISPLAY PANEL

NDC 70771-1770-9 in bottles of 90 tablets

Zituvio® (sitagliptin) Tablets, 25 mg

90 Tablets

Rx Only

NDC 70771-1771-9 in bottles of 90 tablets

Zituvio® (sitagliptin) Tablets, 50 mg

90 Tablets

Rx Only

NDC 70771-1772-9 in bottles of 90 tablets

Zituvio® (sitagliptin) Tablets, 100 mg

90 Tablets

Rx Only